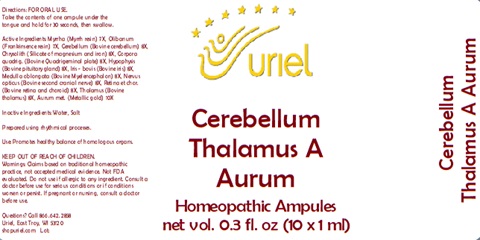 DRUG LABEL: Cerebellum Thalamus A Aurm
NDC: 48951-3050 | Form: LIQUID
Manufacturer: Uriel Pharmacy Inc.
Category: homeopathic | Type: HUMAN OTC DRUG LABEL
Date: 20241216

ACTIVE INGREDIENTS: BOS TAURUS EYE 8 [hp_X]/1 mL; BOS TAURUS NERVE 8 [hp_X]/1 mL; SUS SCROFA THALAMUS 8 [hp_X]/1 mL; GOLD 10 [hp_X]/1 mL; MYRRH 7 [hp_X]/1 mL; FRANKINCENSE 7 [hp_X]/1 mL; BOS TAURUS CEREBELLUM 8 [hp_X]/1 mL; SILICON DIOXIDE 8 [hp_X]/1 mL; BOS TAURUS BRAIN 8 [hp_X]/1 mL; BOS TAURUS PITUITARY GLAND 8 [hp_X]/1 mL
INACTIVE INGREDIENTS: WATER; SODIUM CHLORIDE

Cerebellum Thalamus A Aurum

INDICATIONS AND USAGE

Directions: FOR ORAL USE.

DOSAGE AND ADMINISTRATION

Take the contents of one ampule under the tongue and hold for 30 seconds, then swallow.

ACTIVE INGREDIENT

Active Ingredients: Myrrha (Myrrh resin) 7X, Olibanum (Rubber resin from wood of incense tree) 7X, Cerebellum (Bovine cerebellum) 8X, Chrysolith (Silicate of magnesium and iron) 8X, Corpora quadrig. (Bovine Quadrigeminal plate) 8X, Hypophysis (Bovine pituitary gland) 8X, Iris - bovis (Bovine iris) 8X, Medulla oblongata (Bovine Myelencephalon) 8X, Nervus opticus (Bovine second cranial nerve) 8X, Retina et chor. (Bovine retina and choroid) 8X, Thalamus (Bovine thalamus) 8X, Aurum met. (Metallic gold) 10X

Inactive Ingredients: Water, Salt

Prepared using rhythmical processes.

PURPOSE

Use: Promotes healthy balance of homologous organs.

KEEP OUT OF REACH OF CHILDREN.

WARNINGS

Warnings: Claims based on traditional homeopathic practice, not accepted medical evidence. Not FDA evaluated. Do not use if allergic to any ingredient. Consult a doctor before use for serious conditions or if conditions worsen or persist. If pregnant or nursing, consult a doctor before use.

Questions? Call 866.642.2858
Uriel, East Troy, WI 53120
shopuriel.com Lot: